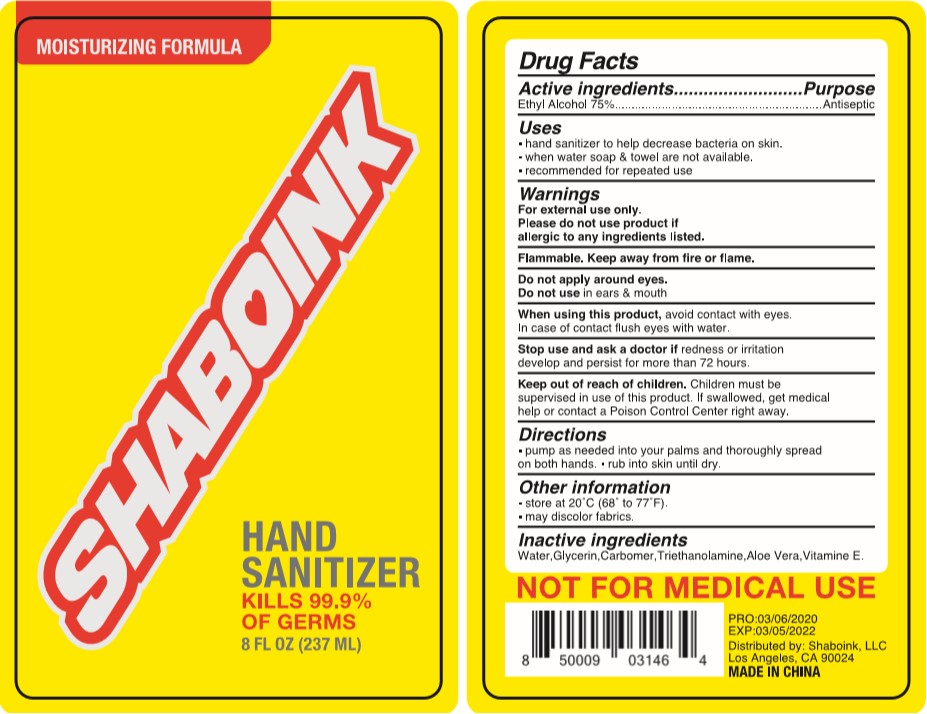 DRUG LABEL: SHABOINK
NDC: 75742-004 | Form: GEL
Manufacturer: Zhejiang Guoyao Jingyue Aerosol Co., Ltd.
Category: otc | Type: HUMAN OTC DRUG LABEL
Date: 20260105

ACTIVE INGREDIENTS: ALCOHOL 75 mL/100 mL
INACTIVE INGREDIENTS: WATER; GLYCERIN; CARBOMER HOMOPOLYMER, UNSPECIFIED TYPE; TROLAMINE; ALOE VERA LEAF; .ALPHA.-TOCOPHEROL SUCCINATE, D-

Active Ingredients

Ethyl Acohol 75%

Purpose

Antiseptic

Uses

- hand sanitizer to help decrease bacteria on skin.
- when water soap & towel are not avaliable.
- recommended for repeated use

Warnings

For external use only.

Please do not use product if allergic to any ingredients listed.

Flammable. Keep away from fire or flame.

Do not apply around eyes.

Do not use in ears & mouth

When using this product, avoid contact with eyes. In case of contact flush eyes with water.

Stop use and ask a doctor if redness or irritation develop and persist for more that 72 hours.

Keep out of reach of children

Children must be supervised in use of this product. if swallowed, get medical help or contact a Poison Control Center right away.

Directions

- pump as needed into your palms and thoroughly spread on both hands
- rub into skin until dry

Inactive ingredients

Water

Glycerin

Carbomer

Triethanolamine

Aloe Vera

Vitamine E

Other information

- store at 20C(8to 77F)
- may discolor fabrics